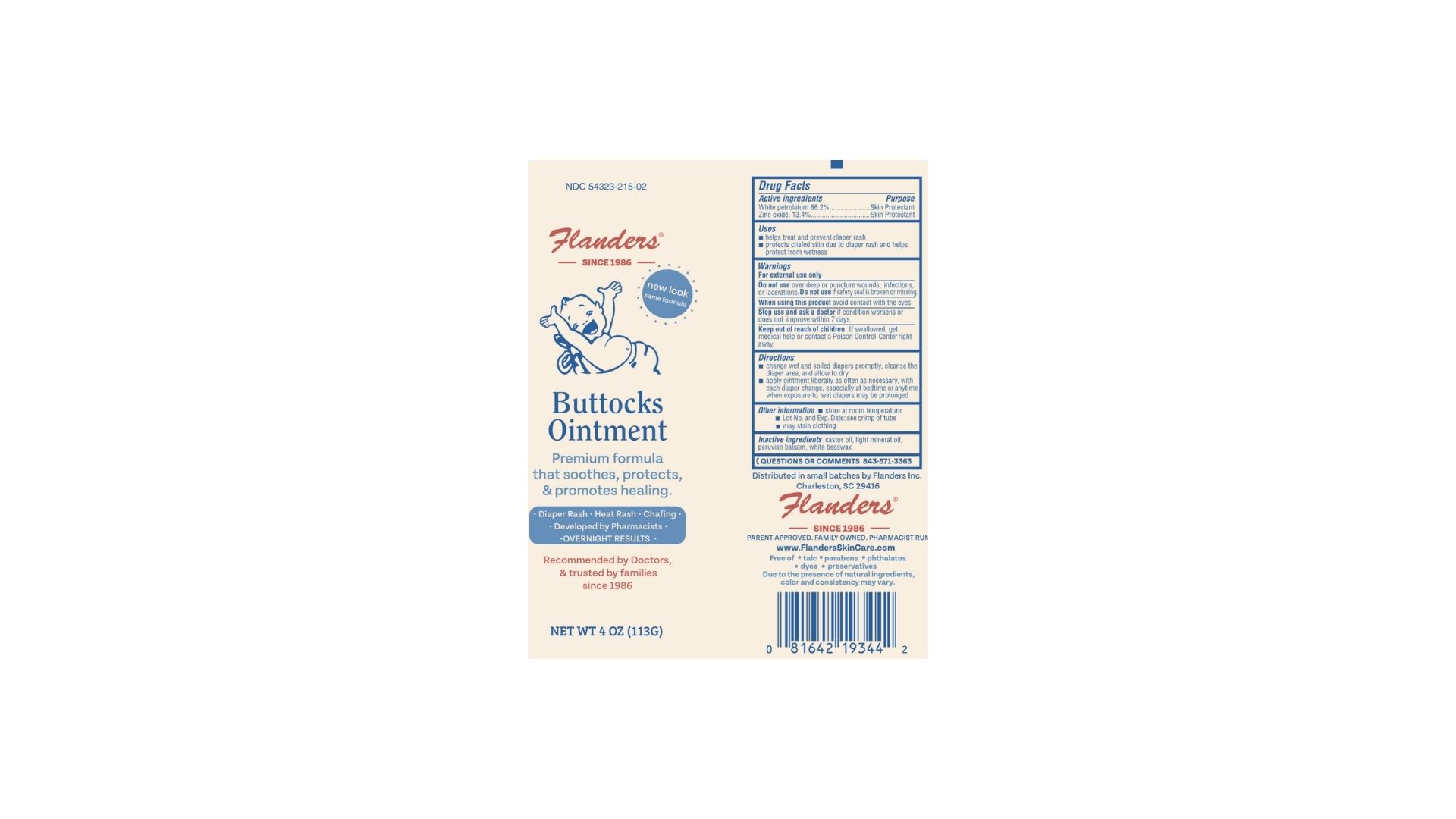 DRUG LABEL: Flanders Buttocks
NDC: 54323-215 | Form: OINTMENT
Manufacturer: Flanders Inc
Category: otc | Type: HUMAN OTC DRUG LABEL
Date: 20241014

ACTIVE INGREDIENTS: PETROLATUM 66.2 g/100 g; ZINC OXIDE 13.4 g/100 g
INACTIVE INGREDIENTS: WHITE WAX; CASTOR OIL; BALSAM PERU; LIGHT MINERAL OIL

Active Ingredients

White Petrolatum 66.2%....................Skin Protectant

Zinc Oxide 13.4%..............................Skin Protectant

Uses

- Helps treat and prevent diaper rash
- protects chafed skin due to diaper rash and helps protect from wetness

Directions

- change wet and soiled diapers promptly, cleanse the diaper area, allow to dry
- apply ointment liberally as necessary, with each diaper change, especailly at bedtime or anytime prolonged exposure to wet diapers may be prolonged

Keep out of reach of children

If swallowed, get medical help or call Poison Control Center right away.

Warnings

For External Use only

Do not Useover deep puncture wounds, infections, or lacerations.

When using this product avoid contact with eyes.

Stop use and ask a doctor if condition worsens or does not improve within 7 days

Inactive Ingredients

castor oil, light mineral oil, peruvian balsam, white beeswax

Purpose

Skin Protectant

Other Information

- store at room temperature
- Lot No. and Exp Date: see crimp of tube
- may stain clothing

Questions or Comments

Call 1-855-NIX-RASH (1-855-649-7472)